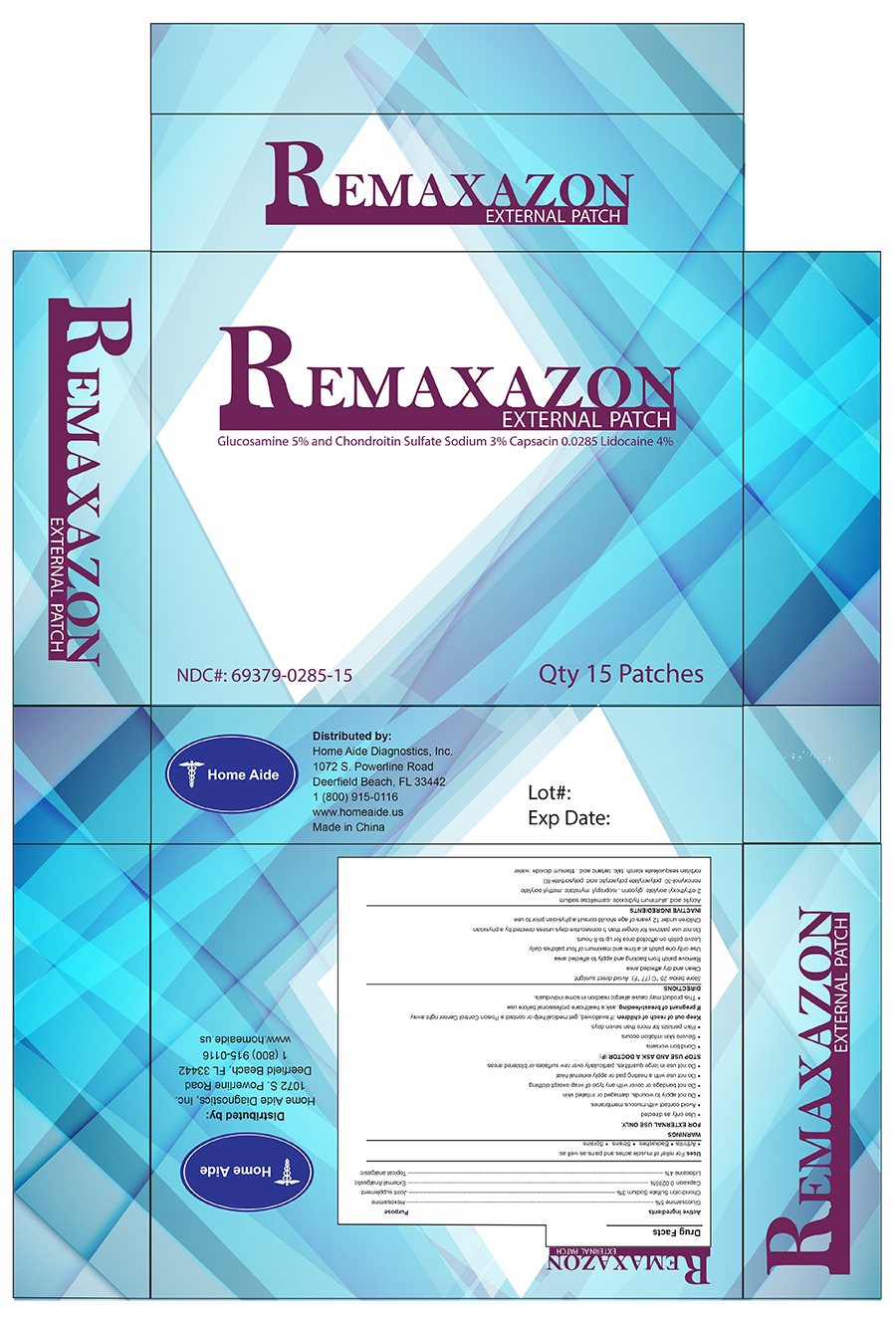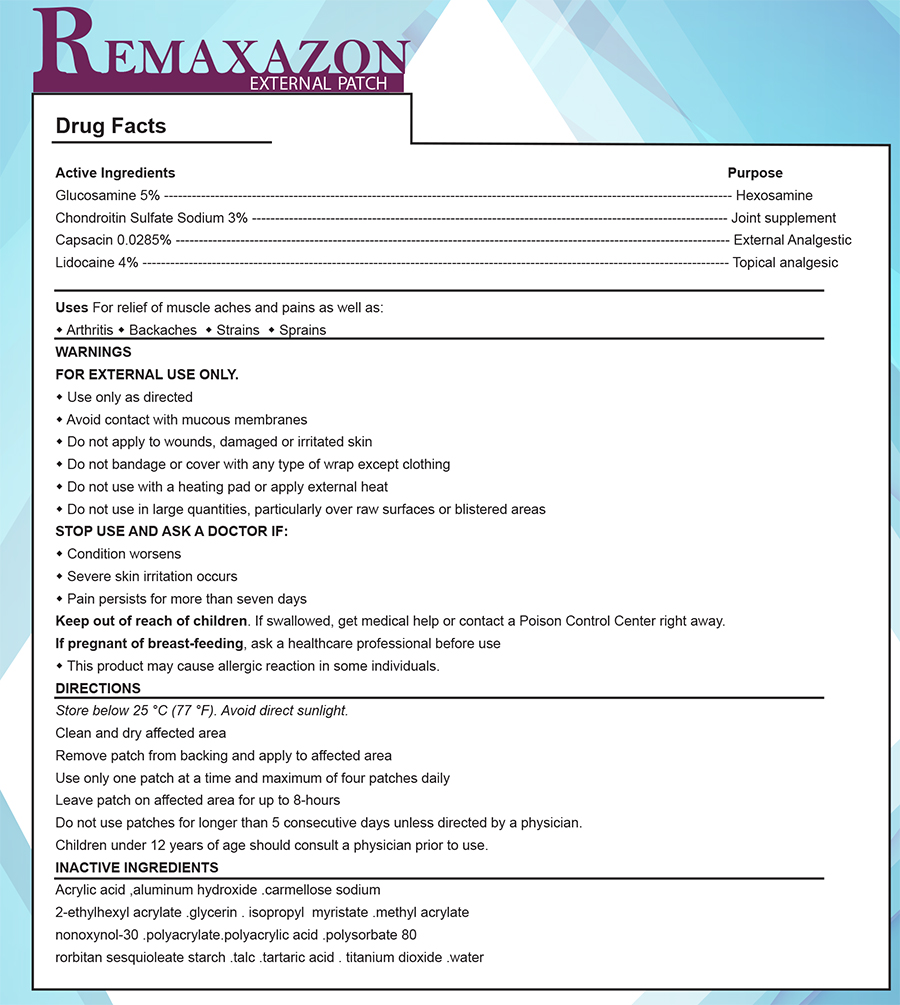 DRUG LABEL: Remaxazon External Patch
NDC: 69379-285 | Form: PATCH
Manufacturer: Home Aide Diagnostics, Inc.
Category: prescription | Type: HUMAN PRESCRIPTION DRUG LABEL
Date: 20150309

ACTIVE INGREDIENTS: CHONDROITIN SULFATE SODIUM (BOVINE) 3 g/100 g; CAPSAICIN .0285 g/100 g; LIDOCAINE 4 g/100 g; GLUCOSAMINE 5 g/100 g

REMAXAZON EXTERNAL PATCH

GENERAL PRECAUTIONS

This product may cause allergic reaction in some individuals.